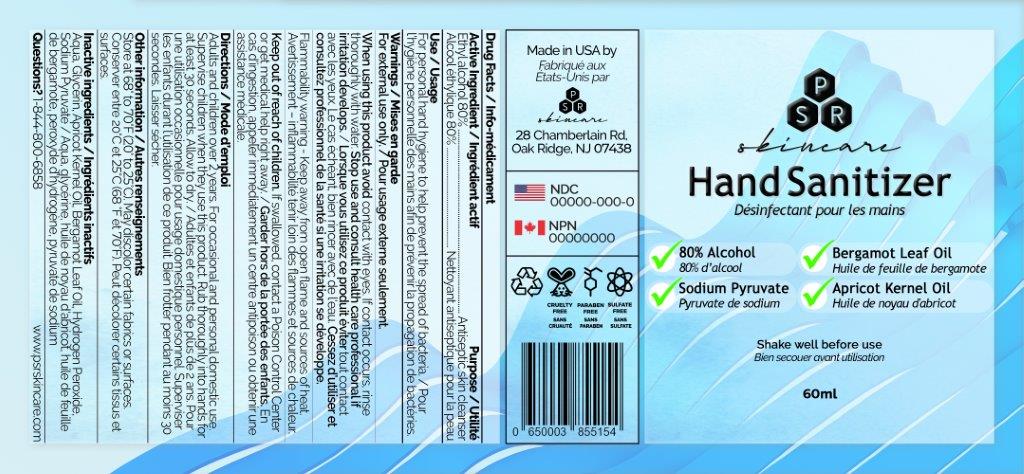 DRUG LABEL: PSR Hand Sanitizer
NDC: 75306-009 | Form: SPRAY
Manufacturer: D-Time Limited Liability Company
Category: otc | Type: HUMAN OTC DRUG LABEL
Date: 20211102

ACTIVE INGREDIENTS: ALCOHOL 80 ng/100 mL
INACTIVE INGREDIENTS: WATER; GLYCERIN; APRICOT KERNEL OIL; BERGAMOT OIL; HYDROGEN PEROXIDE; SODIUM PYRUVATE

Active Ingredient

Ethyl alcohol 80%

Purpose

Antiseptic skin cleanser

Uses

For personal hand hygiene to help prevent the spread of bacteria.

Warnings

For external use only. Flammable. Keep away from heat and flame

When using this product avoid contact with eyes. If contact occurs, rinse thoroughly with water.

Stop use and consult a healthcare professional if irritation develops.

Keep out of reach of children.

If swallowed, get medical help or contact a Poison Control Center right away.

Directions

- Adults and children over 2 years:
- For occasional and personal domestic use
- Supervise children when they use this product ∙
- Spray onto hands and rub thoroughly for at least 30 seconds. Allow to dry

Inactive ingredients

Water (Aqua), Glycerin, Apricot kernel oil, Bergamot leaf oil, Hydrogen peroxide, Sodium pyruvate

Other information

Store at 68° to 70° F (20° to 25° C).
May discolor certain fabrics or surfaces.
Questions? 1-844-800-6858